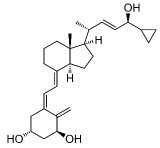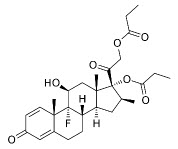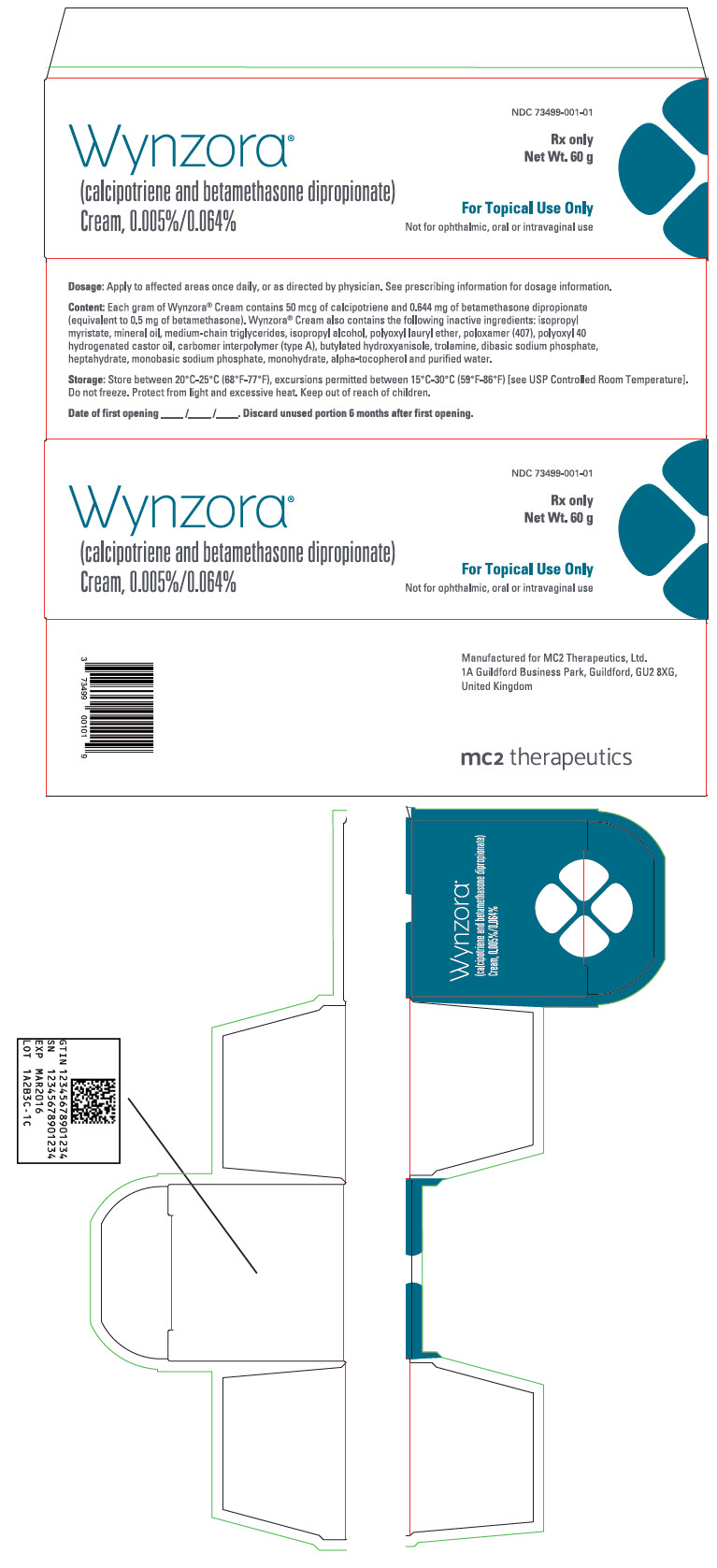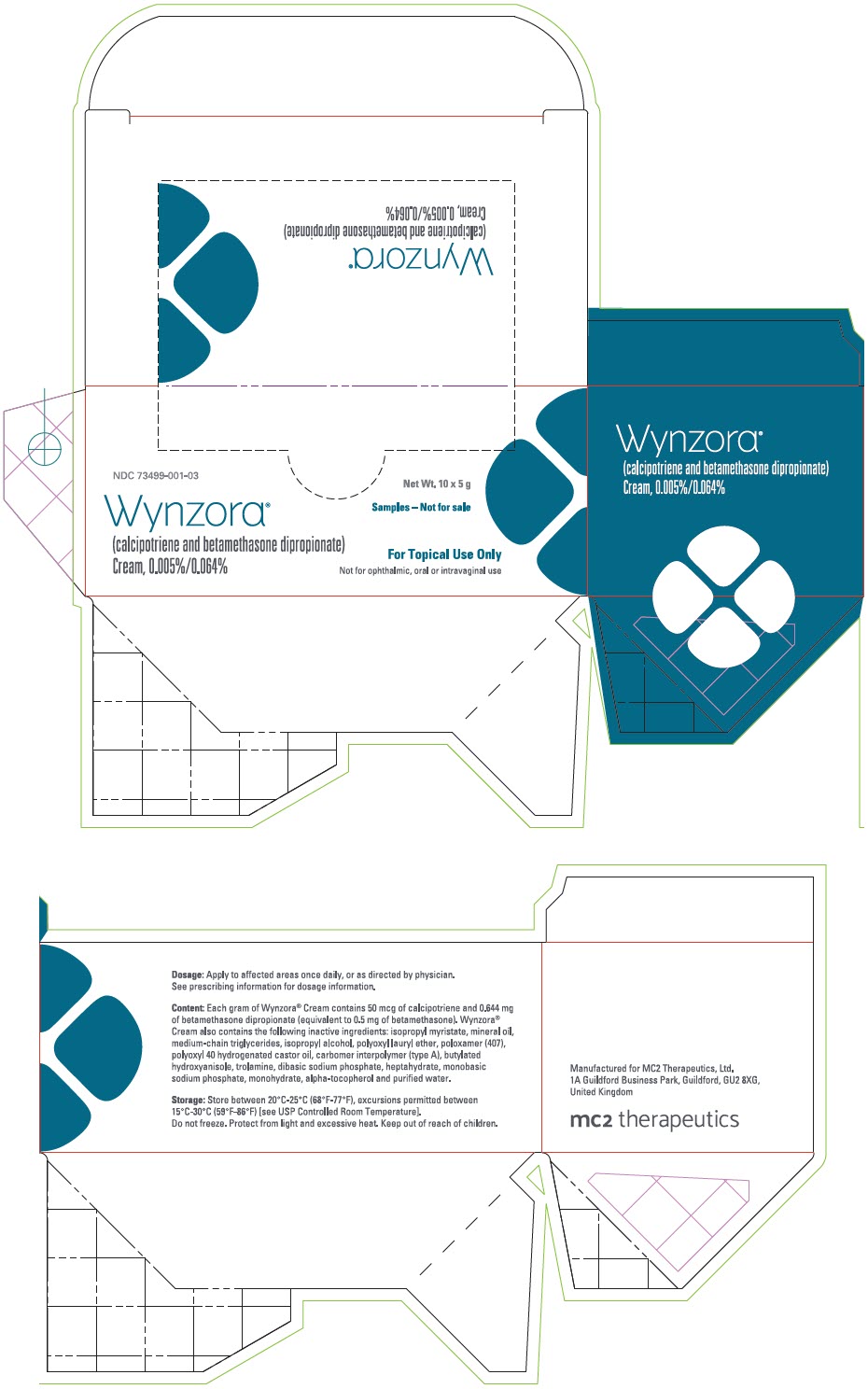 DRUG LABEL: Wynzora
NDC: 73499-001 | Form: CREAM
Manufacturer: MC2 Therapeutics Ltd
Category: prescription | Type: HUMAN PRESCRIPTION DRUG LABEL
Date: 20231129

ACTIVE INGREDIENTS: Calcipotriene 50 ug/1 g; Betamethasone dipropionate 64 mg/1 g
INACTIVE INGREDIENTS: Isopropyl myristate; Mineral oil; Medium-chain triglycerides; Isopropyl alcohol; Laureth-4; Poloxamer 407; Polyoxyl 40 hydrogenated castor oil; Carbomer interpolymer type A (Allyl Sucrose Crosslinked); Butylated hydroxyanisole; Trolamine; Sodium phosphate, dibasic, heptahydrate; Sodium phosphate, monobasic, monohydrate; .Alpha.-Tocopherol, Dl-; Water

HIGHLIGHTS OF PRESCRIBING INFORMATION

These highlights do not include all the information needed to use WYNZORA Cream safely and effectively. See full prescribing information for WYNZORA Cream.
WYNZORA® (calcipotriene and betamethasone dipropionate) cream, for topical use
Initial U.S. Approval: 2020

1 INDICATIONS AND USAGE

WYNZORA Cream is a combination of calcipotriene, a vitamin D analog, and betamethasone dipropionate, a corticosteroid, indicated for the topical treatment of plaque psoriasis in patients 18 years of age and older. (1)

2 DOSAGE AND ADMINISTRATION

- Apply WYNZORA Cream to affected areas once daily for up to 8 weeks. (2)
- Discontinue therapy when control is achieved. (2)
- Do not use more than 100 g per week. (2)
- Do not use with occlusive dressings unless directed by a physician. (2)
- Avoid use on the face, groin, or axillae, or if skin atrophy is present at the treatment site. (2)
- Not for oral, ophthalmic, or intravaginal use. (2)

3 DOSAGE FORMS AND STRENGTHS

Cream: 0.005%/0.064% (3)

4 CONTRAINDICATIONS

None (4)

5 WARNINGS AND PRECAUTIONS

- Hypercalcemia and Hypercalciuria: Hypercalcemia and hypercalciuria have been observed with use of topical calcipotriene. If either occurs, discontinue until parameters of calcium metabolism normalize. (5.1)
- Effects on Endocrine System: Can cause reversible hypothalamicpituitary-adrenal (HPA) axis suppression with the potential for glucocorticosteroid insufficiency during and after withdrawal of treatment. Risk factors include the use of high-potency topical corticosteroid, use over a large surface area, or to areas under occlusion, prolonged use, altered skin barrier, liver failure, and young age. Modify use should HPA axis suppression develop. (5.2)
- Ophthalmic Adverse Reactions: May increase the risk of cataracts and glaucoma. If visual symptoms occur, consider referral to an ophthalmologist. (5.5)

6 ADVERSE REACTIONS

The most common adverse reactions reported by more than 1% of subjects treated with WYNZORA Cream were upper respiratory infection, headache, and application site irritation. (6.1)

To report SUSPECTED ADVERSE REACTIONS, contact MC2 Therapeutics Ltd at 1-800-644-8240 or FDA at 1-800-FDA-1088 or www.fda.gov/medwatch.

FULL PRESCRIBING INFORMATION

1 INDICATIONS AND USAGE

WYNZORA Cream is indicated for the topical treatment of plaque psoriasis in patients 18 years of age and older.

2 DOSAGE AND ADMINISTRATION

Apply WYNZORA Cream to affected areas once daily for up to 8 weeks. Rub in gently to ensure that the plaques are saturated with the cream.

Do not use more than 100 g per week.

Discontinue therapy when control is achieved.

Do not use:

- with occlusive dressings unless directed by a healthcare provider
- on the face, groin, or axillae, or if skin atrophy is present at the treatment site

WYNZORA Cream is not for oral, ophthalmic, or intravaginal use.

3 DOSAGE FORMS AND STRENGTHS

Cream: 0.005%/0.064%.

Each gram of WYNZORA Cream contains 50 mcg of calcipotriene and 0.644 mg of betamethasone dipropionate in a white cream.

4 CONTRAINDICATIONS

None.

5 WARNINGS AND PRECAUTIONS

5.1 Hypercalcemia and Hypercalciuria

Hypercalcemia and hypercalciuria have been observed with use of topical calcipotriene. If hypercalcemia or hypercalciuria develop, discontinue treatment until parameters of calcium metabolism have normalized.

5.2 Effects on Endocrine System

Hypothalamic-Pituitary-Adrenal Axis Suppression

WYNZORA Cream can cause reversible hypothalamic-pituitary-adrenal (HPA) axis suppression with the potential for clinical glucocorticosteroid insufficiency. This may occur during treatment or upon withdrawal of treatment. Factors that predispose a patient to HPA axis suppression include the use of high-potency steroids, large treatment surface areas, prolonged use, use of occlusive dressings, altered skin barrier, liver failure, and young age.

Evaluation for HPA axis suppression may be done by using the adrenocorticotropic hormone (ACTH) stimulation test. If HPA axis suppression is documented, gradually withdraw WYNZORA Cream, reduce the frequency of application, or substitute with a less potent corticosteroid.

The following trial evaluated the effects of WYNZORA Cream on HPA axis suppression:

HPA axis suppression was evaluated in adult subjects (N=27) with extensive psoriasis (including scalp). Adrenal suppression was seen in 6 out of 26 subjects (23%) after 4 weeks of treatment, and in 3 out of 25 subjects (12%) after 8 weeks of treatment [see Clinical Pharmacology (12.2)].

Cushing's Syndrome and Hyperglycemia

Cushing's syndrome and hyperglycemia may occur due to the systemic effects of the topical corticosteroid. These complications generally occur after prolonged exposure to excessively large doses, especially of high-potency topical corticosteroids.

Additional Considerations for Endocrine Adverse Reactions

Pediatric patients may be more susceptible to systemic toxicity due to their larger skin surface to body mass ratios [see Use in Specific Populations (8.4)].

Use of more than one corticosteroid-containing product at the same time may increase total systemic corticosteroid exposure.

5.3 Allergic Contact Dermatitis with Topical Corticosteroids

Allergic contact dermatitis to a topical corticosteroid is usually diagnosed by observing a failure to heal rather than a clinical exacerbation. Such an observation should be corroborated with appropriate diagnostic patch testing.

5.4 Allergic Contact Dermatitis with Topical Calcipotriene

Allergic contact dermatitis has been observed with use of topical calcipotriene. Such an observation should be corroborated with appropriate diagnostic patch testing.

5.5 Ophthalmic Adverse Reactions

Use of topical corticosteroids, including WYNZORA Cream, may increase the risks of glaucoma and posterior subcapsular cataract. Cataracts and glaucoma have been reported with the postmarketing use of topical corticosteroid products [see Adverse Reactions (6.2)].

Avoid contact of WYNZORA Cream with eyes. WYNZORA Cream may cause eye irritation. Advise patients to report any visual symptoms and consider referral to an ophthalmologist for evaluation.

6 ADVERSE REACTIONS

6.1 Clinical Trials Experience

Because clinical trials are conducted under widely varying conditions, adverse reaction rates observed in the clinical trials of a drug cannot be directly compared to rates in the clinical trials of another drug and may not reflect the rates observed in practice.

The rates of adverse reactions given below were reported in a randomized, multicenter, prospective, vehicle and active controlled clinical trial in adult subjects with plaque psoriasis. Subjects applied WYNZORA Cream, calcipotriene/betamethasone dipropionate topical suspension, 0.005%/0.064% or vehicle once daily for 8 weeks. The mean weekly dose of WYNZORA Cream was 33.8 g. A total of 342 subjects were treated with WYNZORA Cream, 337 with calcipotriene/betamethasone dipropionate topical suspension, 0.005%/0.064% and 115 with vehicle. The majority of subjects were White (87%) and male (62%). Approximately 72% were non-Hispanic/Latino. The mean age was 52 years and ages ranged from 18 to 89 years.

The most common adverse reactions reported by ≥1% of subjects treated with WYNZORA Cream and more frequently than vehicle are presented in Table 1 below.

Table 1: Adverse Reactions Through Week 8
Preferred Term | WYNZORA Cream (N=342) | Vehicle Cream (N=115)
Upper Respiratory Infection (URI) [Includes nasopharyngitis, upper respiratory tract infection (URTI), and viral URTI] | 7% | 5%
Headache | 2% | 0%
Application site irritation | 1% | 0%

6.2 Postmarketing Experience

The following adverse reactions have been identified during post-approval use of topical corticosteroids. Because these reactions are reported voluntarily from a population of uncertain size, it is not always possible to reliably estimate their frequency or establish a causal relationship to drug exposure.

Postmarketing reports for local adverse reactions to topical corticosteroids included: atrophy, striae, telangiectasias, itching, dryness, hypopigmentation, perioral dermatitis, secondary infection, and miliaria.

Ophthalmic adverse reactions of cataracts, glaucoma, and increased intraocular pressure, have been reported during use of topical corticosteroids, including topical betamethasone products.

8 USE IN SPECIFIC POPULATIONS

8.1 Pregnancy

Risk Summary

Available data with WYNZORA Cream are not sufficient to evaluate a drug-associated risk for major birth defects, miscarriages, or adverse maternal or fetal outcomes. Although there are no available data on use of the calcipotriene component in pregnant women, systemic exposure to calcipotriene after topical administration of WYNZORA Cream is likely to be low [see Clinical Pharmacology (12.3)].

Observational studies suggest an increased risk of having low birthweight infants with the maternal use of potent or very potent topical corticosteroids (see Data). Advise pregnant women that WYNZORA Cream may increase the potential risk of having a low birth weight infant and to use WYNZORA Cream on the smallest area of skin and for the shortest duration possible.

In animal reproduction studies, oral administration of calcipotriene to pregnant rats during the period of organogenesis resulted in an increased incidence of minor skeletal abnormalities, including enlarged fontanelles and extra ribs (see Data). Oral administration of calcipotriene to pregnant rabbits during the period of organogenesis had no apparent effects on embryo-fetal development. Subcutaneous administration of betamethasone dipropionate to pregnant rats and rabbits during the period of organogenesis resulted in fetal toxicity, including fetal deaths, reduced fetal weight, and fetal malformations (cleft palate and crooked or short tail) (see Data). The available data do not allow the calculation of relevant comparisons between the systemic exposures of calcipotriene and betamethasone dipropionate observed in animal studies to the systemic exposures that would be expected in humans after topical use of WYNZORA Cream.

The background risk of major birth defects and miscarriage in the indicated population is unknown. All pregnancies have a background risk of birth defect, loss, or other adverse outcomes. In the U.S. general population, the estimated background risk of major birth defects and miscarriage in clinically recognized pregnancies is 2% to 4% and 15% to 20%, respectively.

Data

Human Data

Available observational studies in pregnant women did not identify a drug-associated risk of major birth defects, preterm delivery, or fetal mortality with the use of topical corticosteroids of any potency. However, when the dispensed amount of potent or very potent topical corticosteroids exceeded 300 g during the entire pregnancy, maternal use was associated with an increased risk of low birth weight in infants.

Animal Data

Embryo-fetal development studies with calcipotriene were performed by the oral route in rats and rabbits. Pregnant rats received dosages of 0, 6, 18, or 54 mcg/kg/day (0, 36, 108, and 324 mcg/m^2 /day, respectively) on days 6-15 of gestation (the period of organogenesis). There were no apparent effects on maternal survival, behavior, or body weight gain, no effects on litter parameters, and no effects on the incidence of major malformations in fetuses. Fetuses from dams dosed at 54 mcg/kg/day exhibited a significantly increased incidence of minor skeletal abnormalities, including enlarged fontanelles and extra ribs.

Pregnant rabbits were dosed daily with calcipotriene at exposures of 0, 4, 12, or 36 mcg/kg/day (0, 48, 144, and 432 mcg/m^2 /day, respectively) on days 6-18 of gestation (the period of organogenesis). Mean maternal body weight gain was reduced in animals dosed at 12 or 36 mcg/kg/day. The incidence of fetal deaths was increased in the group dosed at 36 mcg/kg/day; reduced fetal weight was also observed in this group. The incidence of major malformations among fetuses was not affected. An increase in the incidence of minor skeletal abnormalities, including incomplete ossification of sternebrae, pubic bones, and forelimb phalanges, was observed in the group dosed at 36 mcg/kg/day.

Embryo-fetal development studies with betamethasone dipropionate were performed via subcutaneous injection in mice and rabbits. Pregnant mice were administered doses of 0, 156, 625, or 2500 mcg/kg/day (0, 468, 1875, and 7500 mcg/m^2 /day, respectively) on days 7 through 13 of gestation (the period of organogenesis). Betamethasone dipropionate induced fetal toxicity, including fetal deaths, reduced fetal weight, malformations (increased incidence of the cleft palate and crooked or short tail), and minor skeletal abnormalities (delayed ossification of vertebra and sternebrae). Fetal toxicity was observed at the lowest exposure that was evaluated (156 mcg/kg/day).

Pregnant rabbits were injected subcutaneously at dosages of 0, 0.625, 2.5, and 10 mcg/kg/day (0, 7.5, 30, and 120 mcg/m^2 /day, respectively) on days 6 through 18 of gestation (the period of organogenesis). Betamethasone dipropionate induced fetal toxicity, including fetal deaths, reduced fetal weight, external malformations (including malformed ears, cleft palate, umbilical hernia, kinked tail, club foot, and club hand), and skeletal malformations (including absence of phalanges of the first digit and cranial dysplasia) at dosages of 2.5 mcg/kg/day and above.

Calcipotriene was evaluated for effects on peri- and post-natal development when orally administered to pregnant rats at dosages of 0, 6, 18 or 54 mcg/kg/day (0, 36, 108, and 324 mcg/m^2 /day, respectively) from gestation day 15 through day 20 postpartum. No remarkable effects were observed on any parameter, including survival, behavior, body weight, litter parameters, or the ability to nurse or rear pups.

Betamethasone dipropionate was evaluated for effects on peri- and post-natal development when orally administered to pregnant rats at dosages of 0, 100, 300, and 1000 mcg/kg/day (0, 600, 1800, and 6000 mcg/m^2 /day, respectively) from gestation day 6 through day 20 postpartum. Mean maternal body weight was significantly reduced on gestation day 20 in animals dosed at 300 and 1000 mcg/kg/day. The mean duration of gestation was slightly, but statistically significantly, increased at 100, 300, and 1000 mcg/kg/day. The mean percentage of pups that survived to day 4 was reduced in relation to dosage. On lactation day 5, the percentage of pups with a reflex to right themselves when placed on their back was significantly reduced at 1000 mcg/ kg/day. No effects on the ability of pups to learn were observed, and the ability of the offspring of treated rats to reproduce was not affected.

8.2 Lactation

Risk Summary

There is no information regarding the presence of topically administered calcipotriene and betamethasone dipropionate in human milk, the effects on the breastfed infant, or the effects on milk production. Concentrations of calcipotriene in plasma are low after topical administration, and therefore, concentrations in human milk are likely to be low [see Clinical Pharmacology (12.3)].

It is not known whether topically administered calcipotriene or corticosteroids could result in sufficient systemic absorption to produce detectable quantities in human milk. The developmental and health benefits of breastfeeding should be considered along with the mother's clinical need for WYNZORA Cream and any potential adverse effects on the breastfed child from WYNZORA Cream or from the underlying maternal condition.

Clinical Considerations

To minimize potential exposure to the breastfed infant via breast milk, use WYNZORA Cream on the smallest area of skin and for the shortest duration possible while breastfeeding. Advise breastfeeding women not to apply WYNZORA Cream directly to the nipple and areola to avoid direct infant exposure.

8.4 Pediatric Use

Safety and effectiveness of the use of WYNZORA Cream in adolescents and pediatric patients under the age of 18 years have not been established.

Because of a higher ratio of skin surface area to body mass, pediatric patients are at a greater risk than adults of systemic toxicity when treated with topical corticosteroids. Pediatric patients are, therefore, also at greater risk of HPA axis suppression and adrenal insufficiency with the use of topical corticosteroids including WYNZORA Cream [see Clinical Pharmacology (12.2)].

Systemic toxicities such as Cushing's syndrome, linear growth retardation, delayed weight gain, and intracranial hypertension have been reported in pediatric patients, especially those with prolonged exposure to large doses of high potency topical corticosteroids. Local adverse reactions including striae have also been reported with use of topical corticosteroids in pediatric patients.

8.5 Geriatric Use

The trial included 66 subjects ≥ 65 years of age treated with WYNZORA Cream.

No overall differences in safety or effectiveness of WYNZORA Cream were observed between these subjects and younger subjects. All other reported clinical experience has not identified any differences in response between elderly and younger patients. However, greater sensitivity of some older individuals cannot be ruled out.

11 DESCRIPTION

WYNZORA (calcipotriene and betamethasone dipropionate) Cream contains anhydrous calcipotriene and betamethasone dipropionate intended for topical use.

Calcipotriene is a synthetic vitamin D3 analog.

Chemically, calcipotriene is (5Z,7E,22E,24S)-24-Cyclopropyl-9,10-secochola-5,7,10(19),22 tetraene-1α,3β,24-triol, with the empirical formula C27H40O3, a molecular weight of 412.6, and the following structural formula:

Calcipotriene is a white or almost white powder. It is insoluble in water, freely soluble in ethanol and slightly soluble in methylene chloride.

Betamethasone dipropionate is a synthetic corticosteroid.

Betamethasone dipropionate has the chemical name Pregna-1,4-diene-3,20-dione,9-fluoro-11-hydroxy-16-methyl-17,21-bis(1-oxypropoxy)-,(11β,16β), with the empirical formula C28H37FO7, a molecular weight of 504.6, and the following structural formula:

Betamethasone dipropionate is a white to almost white crystalline powder. It is practically insoluble in water, freely soluble in acetone and in methylene chloride, sparingly soluble in alcohol.

Each gram of WYNZORA Cream contains 50 mcg of calcipotriene and 0.644 mg of betamethasone dipropionate (equivalent to 0.5 mg of betamethasone). WYNZORA Cream also contains the following inactive ingredients: isopropyl myristate, mineral oil, medium-chain triglycerides, isopropyl alcohol, polyoxyl lauryl ether, poloxamer (407), polyoxyl 40 hydrogenated castor oil, carbomer interpolymer (type A), butylated hydroxyanisole, trolamine, dibasic sodium phosphate, heptahydrate, monobasic sodium phosphate, monohydrate, alpha-tocopherol and purified water.

12 CLINICAL PHARMACOLOGY

12.1 Mechanism of Action

WYNZORA Cream combines the pharmacological effects of calcipotriene as a synthetic vitamin D3 analog and betamethasone dipropionate as a synthetic corticosteroid. However, while their pharmacologic and clinical effects are known, the exact mechanisms of their actions in plaque psoriasis are unknown.

12.2 Pharmacodynamics

Vasoconstriction:

In a vasoconstrictor trial in healthy subjects, the skin blanching response of WYNZORA Cream was consistent with a mid-strength corticosteroid when compared with other topical corticosteroids. However, similar blanching scores do not necessarily imply therapeutic equivalence.

Hypothalamic-Pituitary-Adrenal (HPA) Axis Suppression:

HPA axis suppression was evaluated in adult subjects with extensive psoriasis involving 20-30% of the body surface area (including scalp). Treatment consisted of once daily application of WYNZORA Cream to the body (including scalp involvement in 75% of the subjects) for up to 8 weeks. Adrenal suppression indicated by 30-minute post-stimulation serum cortisol level of ≤18 mcg/dL was seen in 6 out of 26 subjects (23%) after 4 weeks of treatment, and in 3 out of 25 subjects (12%; one subject with continued suppression from Week 4 and two additional subjects) after 8 weeks of treatment.

There was no trend towards decreasing cortisol levels post-ACTH stimulation with increasing systemic concentration of betamethasone 17-propionate (B17P) measured as AUC0-7 or Cmax or increasing average weekly amount of WYNZORA Cream used.

Effects on Calcium Metabolism:

The effects on calcium metabolism of once daily application of WYNZORA Cream to the body (including scalp involvement in 75% of subjects) for up to 8 weeks were also examined and no cases of hypercalcemia and no clinically relevant changes in urine calcium were reported.

12.3 Pharmacokinetics

Absorption

The pharmacokinetics of WYNZORA Cream was investigated in adult subjects in the same study as described above [see Clinical Pharmacology (12.2)]. Their mean ± SD total body surface area involvement was 25 ± 5 % and 74% of the subjects presented with scalp involvement and with a mean ± SD scalp involvement of 52 ± 40 %. The mean ± SD weekly dose during the 8 weeks of treatment was 79 ± 30 g.

Plasma concentrations of calcipotriene and betamethasone dipropionate and their major metabolites were measured after 4 weeks and 8 weeks of once daily application of WYNZORA Cream.

In most samples, concentrations of the four analytes were below or close to lower limit of quantification (LOQ). One of 27 (4%) subjects had quantifiable levels of calcipotriene at Week 4 and the Cmax and AUC0-7 were 30 pg/mL and 229 pg*h/mL, respectively. For the major metabolite of calcipotriene, MC1080, 3 of 27 (11%) subjects had quantifiable levels at Week 4. The mean ± SD Cmax and AUC0-7 were 30 ± 4 pg/mL and 224 ± 16 pg*h/mL, respectively. No subjects had quantifiable levels of calcipotriene or MC1080 at Week 8.

There were 3 of 27 subjects (11%) with quantifiable levels of betamethasone dipropionate at Week 4. The mean ± SD of Cmax and AUC0-7 were 22 ± 9 pg/mL and 160 ± 36 pg*h/mL, respectively. The major metabolite of betamethasone dipropionate, B17P, was quantifiable in 13 of 27 subjects (48%) at Week 4. The mean ± SD Cmax and AUC0-7 were 96 ± 234 pg/mL and 419 ± 646 pg*h/mL, respectively. No subjects had quantifiable levels of betamethasone dipropionate at Week 8, whereas 7 of 19 (37%) subjects had quantifiable levels of B17P. The mean ± SD Cmax and AUC0-7 were 31 ± 29 pg/mL and 205 ± 142 pg*h/mL, respectively.

Metabolism

Calcipotriene:

Calcipotriene metabolism following systemic uptake is rapid and occurs in the liver. The primary metabolites of calcipotriene are less potent than the parent compound.

Calcipotriene is metabolized to MC1046 (the α,ß-unsaturated ketone analog of calcipotriene), which is metabolized further to MC1080 (a saturated ketone analog). MC1080 is the major metabolite in plasma. MC1080 is slowly metabolized to calcitroic acid.

Betamethasone dipropionate:

Betamethasone dipropionate is metabolized by hydrolysis to betamethasone 17-propionate and betamethasone, including the 6ß-hydroxy derivatives of those compounds. Betamethasone17-propionate (B17P) is the primary metabolite.

13 NONCLINICAL TOXICOLOGY

13.1 Carcinogenesis, Mutagenesis, Impairment of Fertility

When calcipotriene was applied topically to mice for up to 24 months at dosages of 3, 10, and 30 mcg/kg/day (corresponding to 9, 30, and 90 mcg/m^2/day), no significant changes in tumor incidence were observed when compared to control.

A 104-week oral carcinogenicity study was conducted with calcipotriene in male and female rats at doses of 1, 5 and 15 mcg/kg/day (corresponding to dosages of approximately 6, 30, and 90 mcg/m^2/day). Beginning week 71, the dosage for high-dose animals of both genders was reduced to 10 mcg/kg/day (corresponding to a dosage of approximately 60 mcg/m^2/day). A treatment-related increase in benign C-cell adenomas was observed in the thyroid of females that received 15 mcg/kg/day. A treatment-related increase in benign pheochromocytomas was observed in the adrenal glands of males that received 15 mcg/kg/day. No other statistically significant differences in tumor incidence were observed when compared to control. The relevance of these findings to patients is unknown.

When betamethasone dipropionate was applied topically to CD-1 mice for up to 24 months at dosages approximating 1.3, 4.2, and 8.5 mcg/kg/day in females, and 1.3, 4.2, and 12.9 mcg/kg/day in males (corresponding to dosages of up to approximately 26 mcg/m^2/day and 39 mcg/m^2/day, in females and males, respectively), no significant changes in tumor incidence were observed when compared to control.

When betamethasone dipropionate was administered via oral gavage to male and female Sprague Dawley rats for up to 24 months at dosages of 20, 60, and 200 mcg/kg/day (corresponding to dosages of approximately 120, 360, and 1200 mcg/m^2/day), no significant changes in tumor incidence were observed when compared to control.

Calcipotriene did not elicit any genotoxic effects in the Ames mutagenicity assay, the mouse lymphoma TK locus assay, the human lymphocyte chromosome aberration test, or the mouse micronucleus test. Betamethasone dipropionate did not elicit any genotoxic effects in the Ames mutagenicity assay, the mouse lymphoma TK locus assay, or in the rat micronucleus test.

Studies in rats with oral doses of up to 54 mcg/kg/day (324 mcg/m^2/day) of calcipotriene indicated no impairment of fertility or general reproductive performance. Studies in male rats at oral doses of up to 200 mcg/kg/day (1200 mcg/m^2/day), and in female rats at oral doses of up to 1000 mcg/kg/day (6000 mcg/m^2/day), of betamethasone dipropionate indicated no impairment of fertility.

14 CLINICAL STUDIES

The safety and efficacy of WYNZORA Cream were evaluated in a randomized, multicenter, vehicle and active-comparator controlled, clinical trial (NCT03308799) in adult subjects with mild to moderate plaque psoriasis. In the trial, 794 subjects were randomized to 1 of 3 treatment groups: WYNZORA Cream, vehicle cream, or calcipotriene/betamethasone dipropionate topical suspension, 0.005%/0.064%. The majority of subjects in the trial (81.7%) had disease of moderate severity at baseline, while 18.3% of subjects had disease of mild severity. Disease severity was determined by a 5-grade Physician's Global Assessment (PGA) scale.

The primary efficacy endpoint was the proportion of subjects with treatment success at Week 8. Treatment success was defined as at least a 2-grade improvement from baseline in the PGA score and an PGA score equating to "clear" or "almost clear". Other evaluated outcomes included reduction in itch as defined by at least a 4-point improvement in the 11-point peak pruritus numeric rating scale (NRS) from baseline to Week 4. Table 2 presents the primary efficacy results.

Table 2: Primary Efficacy Outcome at Week 8
 | WYNZORA Cream (N=342) | Vehicle Cream (N=115)
PGA of Clear or Almost Clear And ≥2-grade Improvement | 37.4% | 3.7%
Difference from Vehicle (95% CI) | 33.7% (27.4%, 40.0%)

WYNZORA Cream was non-inferior to calcipotriene/betamethasone dipropionate topical suspension, 0.005%/0.064% for the primary endpoint of treatment success at Week 8 [Difference (95% CI): 14.6% (7.6%, 21.6%)].

Among subjects who had at least a peak pruritus NRS score of 4 at baseline, there was a higher percentage of subjects that achieved at least a 4-point improvement from baseline on the peak pruritus NRS score at Week 4 in the WYNZORA Cream group compared to the vehicle cream group (60.3% vs. 21.4%).

16 HOW SUPPLIED/STORAGE AND HANDLING

WYNZORA® (calcipotriene and betamethasone dipropionate) Cream, 0.005%/0.064%, is a white cream. Each gram of cream contains 50 mcg of anhydrous calcipotriene and 0.644 mg of betamethasone dipropionate. It is available as 60 g tubes individually packaged (NDC 73499-001-01).

STORAGE AND HANDLING

Store between 20°C-25°C (68°F-77°F); excursions permitted between 15°C-30°C (59°F-86°F). [See USP controlled room temperature.]

Do not freeze. Protect from light and excessive heat.

Unused product should be discarded six months after the tube has been opened.

17 PATIENT COUNSELING INFORMATION

Advise the patient to read the FDA-approved patient labeling (Patient Information).

Administration Instructions

- Instruct patients not to use more than 100 grams per week.
- Instruct patients to discontinue therapy when control is achieved unless directed otherwise by the healthcare provider.
- Advise patients to avoid use of WYNZORA Cream on the face, underarms, groin or eyes.
- Advise patients not to occlude the treatment area with a bandage or other covering unless directed by the healthcare provider.
- Instruct patients to wash hands after application.

Local Reactions and Skin Atrophy

Advise patients that local reactions and skin atrophy are more likely to occur with occlusive use, prolonged use or use of higher potency corticosteroids.

Hypercalcemia and Hypercalciuria

Advise patients that hypercalcemia and hypercalciuria may occur with the use of WYNZORA Cream [see Warnings and Precautions (5.1)].

HPA Axis Suppression, Cushing's Syndrome, and Hyperglycemia

Advise patients that WYNZORA Cream can cause HPA access suppression, Cushing's syndrome, and/or hyperglycemia [see Warnings and Precautions (5.2)].

Ophthalmic Adverse Reactions

Advise patients to avoid contact of WYNZORA Cream with eyes and to report any visual symptoms [see Warnings and Precautions (5.5)].

Possible Avoidance of Other Products Containing Calcipotriene or a Corticosteroid

Instruct patients not to use other products containing calcipotriene or a corticosteroid with WYNZORA Cream without first talking to the healthcare provider.

Pregnancy and Lactation

- Advise pregnant women that WYNZORA Cream may increase the potential risk of having a low birth weight infant and to use WYNZORA Cream on the smallest area of skin and for the shortest duration possible [see Use in Specific Populations (8.1)].
- Advise breastfeeding women not to apply WYNZORA Cream directly to the nipple and areola to avoid direct infant exposure [see Use in Specific Populations (8.2)].

Manufactured for:
MC2 Therapeutics, Ltd. 1A Guildford Business Park, Guildford, GU2 8XG, United Kingdom

PATIENT INFORMATION
WYNZORA® (win-ZOR-uh)
(calcipotriene and betamethasone dipropionate)
Cream

Important information: WYNZORA® Cream is for use on the skin only (topical use only). Do not get WYNZORA® Cream near or in your mouth, eyes, or vagina.

There are other medicines that contain the same medicine that is in WYNZORA® Cream and are used to treat plaque psoriasis. Do not use other products containing calcipotriene or a corticosteroid medicine with WYNZORA® Cream without talking to your healthcare provider first.

What is WYNZORA® Cream?
WYNZORA® Cream is a prescription medicine used on the skin (topical) to treat plaque psoriasis in people 18 years of age and older.
It is not known if WYNZORA® Cream is safe and effective in children under 18 years of age.

Before using WYNZORA® Cream, tell your healthcare provider about all of your medical conditions, including if you:

- have a calcium metabolism disorder.
- have thinning skin (atrophy) at the treatment site.
- are pregnant or plan to become pregnant. It is not known if WYNZORA® Cream will harm your unborn baby. WYNZORA® Cream may increase your chance of having a low birth weight baby. If you use WYNZORA® Cream during pregnancy, use WYNZORA® Cream on the smallest area of the skin and for the shortest time needed.
- are breastfeeding or plan to breastfeed. It is not known if WYNZORA® Cream passes into your breast milk. Breastfeeding women should use WYNZORA® Cream on the smallest area of the skin and for the shortest time needed. Do not apply WYNZORA® Cream directly to the nipple and areola to avoid contact with your baby.

Tell your healthcare provider about all the medicines you take, including prescription and over-the-counter medicines, vitamins and herbal supplements.

How should I use WYNZORA® Cream?

- Use WYNZORA® Cream exactly as prescribed by your healthcare provider.
- Your healthcare provider should tell you how much WYNZORA® Cream to use and where to use it.
- Apply WYNZORA® Cream to affected areas 1 time a day for up to 8 weeks. You should stop treatment when your plaque psoriasis is under control unless your healthcare provider gives you other instructions.
- You should not use more than 100 grams of WYNZORA® Cream in 1 week.
- Do not use WYNZORA® Cream longer than prescribed. Using too much WYNZORA® Cream, or using it too often or for too long, can increase your risk for having serious side effects.
- Do not use WYNZORA® Cream in the mouth, eyes, or vagina.
- Do not use WYNZORA® Cream on your face, groin, or armpits, or if you have thinning of your skin (atrophy) at the treatment site.
- If you accidentally get WYNZORA® Cream on your face or in your eyes wash the area with water right away.
- Wash your hands well after applying WYNZORA® Cream.
- Do not bandage or cover the treated skin area, unless instructed by your healthcare provider.

Applying WYNZORA® Cream:

- Remove the cap and check that the aluminum seal covers the opening on the top of the tube before the first use. To break the seal, turn the cap over and poke a hole through the seal.
- Gently rub WYNZORA® Cream all the way in to make sure that the plaques are well covered with the cream.

What are the possible side effects of WYNZORA® Cream?
WYNZORA® Cream may cause serious side effects, including:

- Too much calcium in your blood or urine. Your healthcare provider may tell you to stop or temporarily stop treatment with WYNZORA® Cream if you have too much calcium in your blood or urine.
- WYNZORA® Cream can pass through your skin. Too much WYNZORA® Cream passing through your skin can cause your adrenal glands to stop working properly. Your healthcare provider may do blood tests to check for adrenal gland problems. Your healthcare provider may tell you to stop or temporarily stop treatment with WYNZORA® Cream.
- Cushing's syndrome, a condition that happens when your body is exposed to large amounts of the hormone cortisol.
- High blood sugar (hyperglycemia).
- Skin problems. Tell your healthcare provider if you have any skin problems, including:

- thinning of your skin
- burning
- inflammation
- itching
- irritation

- dryness
- changes in skin color
- redness
- infection
- raised bumps on your skin

- Eye problems. Using WYNZORA® Cream may increase your chance of getting cataracts and glaucoma. Do not get WYNZORA® Cream in your eyes because it may cause eye irritation. Tell your healthcare provider if you have blurred vision or other vision problems during treatment with WYNZORA® Cream.

The most common side effects of WYNZORA® Cream include upper respiratory infection, headache and irritation at the treatment site.
Call your doctor for medical advice about side effects. You may report side effects to FDA at 1- 800-FDA-1088.

How should I store WYNZORA® Cream?

- Store WYNZORA® Cream at room temperature between 68°F to 77°F (20°C to 25°C) with the cap on the tube tightly closed.
- Do not freeze and protect WYNZORA® Cream from light and excessive heat.
- Keep WYNZORA® Cream out of the light.
- Throw away (discard) unused WYNZORA® Cream 6 months after it has been opened.

Keep WYNZORA® Cream and all medicines out of the reach of children.

General information about WYNZORA® Cream
Medicines are sometimes prescribed for purposes other than those listed in a Patient Information leaflet. Do not use WYNZORA® Cream for a condition for which it was not prescribed. Do not give WYNZORA® Cream to other people, even if they have the same symptoms you have. It may harm them. You can ask your pharmacist or healthcare provider for information about WYNZORA® Cream that is written for health professionals.

What are the ingredients in WYNZORA® Cream?
Active ingredients: calcipotriene and betamethasone dipropionate
Inactive ingredients: isopropyl myristate, mineral oil, medium-chain triglycerides, isopropyl alcohol, polyoxyl lauryl ether, poloxamer (407), polyoxyl 40 hydrogenated castor oil, carbomer interpolymer (type A), butylated hydroxyanisole, trolamine, dibasic sodium phosphate, heptahydrate, monobasic sodium phosphate, monohydrate, alpha-tocopherol and purified water.
Manufactured for: MC2 Therapeutics, Ltd. 1A Guildford Business Park, Guildford, GU2 8XG, United Kingdom.
For more information, go to www.wynzora.com or call 1-800-644-8240

This Patient Information has been approved by the U.S. Food and Drug Administration

Issued: 11/2023

PRINCIPAL DISPLAY PANEL - 60 g Tube Carton

Wynzora®
(calcipotriene and betamethasone dipropionate)
Cream, 0.005%/0.064%

NDC 73499-001-01

Rx only
Net Wt. 60 g

For Topical Use Only
Not for ophthalmic, oral or intravaginal use

PRINCIPAL DISPLAY PANEL - 5 g Tube Carton

NDC 73499-001-03

Wynzora®
(calcipotriene and betamethasone dipropionate)
Cream, 0.005%/0.064%

Net Wt. 10 x 5 g

Samples – Not for sale

For Topical Use Only
Not for ophthalmic, oral or intravaginal use